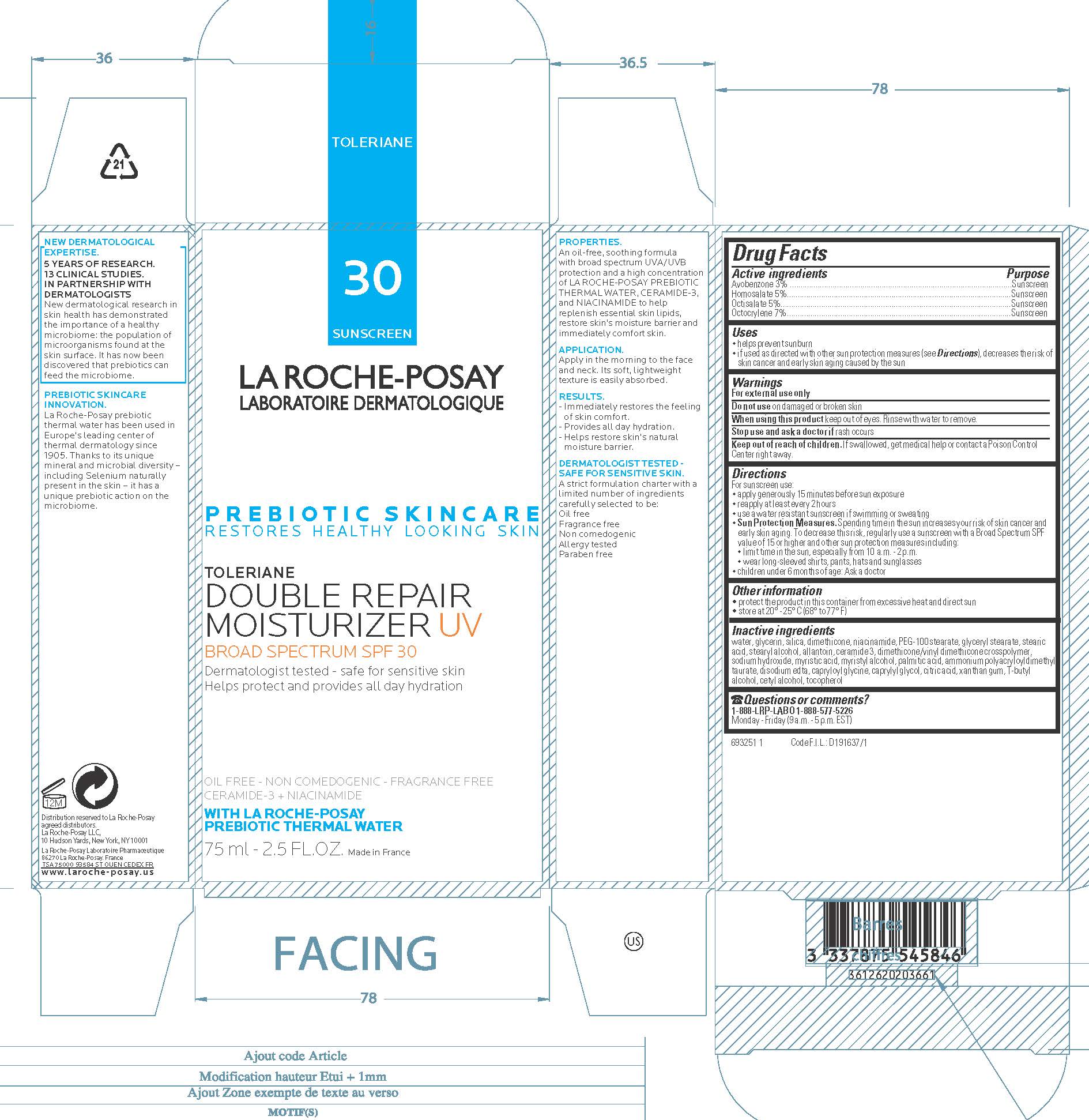 DRUG LABEL: La Roche Posay Laboratoire Dermatologique Toleriane Double Repair UV Broad Spectrum SPF 30 Sunscreen
NDC: 69625-583 | Form: LOTION
Manufacturer: Cosmetique Active Production
Category: otc | Type: HUMAN OTC DRUG LABEL
Date: 20240408

ACTIVE INGREDIENTS: AVOBENZONE 30 mg/1 mL; HOMOSALATE 50 mg/1 mL; OCTISALATE 50 mg/1 mL; OCTOCRYLENE 70 mg/1 mL
INACTIVE INGREDIENTS: WATER; GLYCERIN; SILICON DIOXIDE; DIMETHICONE; NIACINAMIDE; PEG-100 STEARATE; GLYCERYL MONOSTEARATE; STEARIC ACID; STEARYL ALCOHOL; ALLANTOIN; CERAMIDE 3; DIMETHICONE/VINYL DIMETHICONE CROSSPOLYMER (SOFT PARTICLE); SODIUM HYDROXIDE; MYRISTIC ACID; MYRISTYL ALCOHOL; PALMITIC ACID; EDETATE DISODIUM ANHYDROUS; CAPRYLOYL GLYCINE; CAPRYLYL GLYCOL; CITRIC ACID MONOHYDRATE; XANTHAN GUM; TERT-BUTYL ALCOHOL; CETYL ALCOHOL; TOCOPHEROL

Drug Facts

Active ingredients

Avobenzone 3%

Homosalate 5%

Octisalate 5%

Octocrylene 7%

Purpose

Sunscreen

Uses

• helps prevent sunburn
• if used as directed with other sun protection measures (see Directions), decreases the risk of skin cancer and early skin aging caused by the sun

Warnings

For external use only

Do not use

on damaged or broken skin

When using this product

keep out of eyes. Rinse with water to remove.

Stop use and ask a doctor if

rash occurs

Keep out of reach of children.

If swallowed, get medical help or contact a Poison Control Center right away.

Directions

For sunscreen use:
● shake well

● apply liberally 15 minutes before sun exposure
● reapply at least every 2 hours
● use a water resistant sunscreen if swimming or sweating
● Sun Protection Measures. Spending time in the sun increases your risk of skin cancer and early skin aging. To decrease this risk, regularly use a sunscreen with a Broad Spectrum SPF value of 15 or higher and other sun protection measures including:
● limit time in the sun, especially from 10 a.m. – 2 p.m.
● wear long-sleeved shirts, pants, hats, and sunglasses
● children under 6 months of age: Ask a doctor

Other information

protect the product in this container from excessive heat and direct sun

Inactive ingredients

water, glycerin, silica, dimethicone, niacinamide, PEG-100 stearate, glyceryl stearate, stearic acid, allantoin, ceramide 3, dimethicone/vinyl dimethicone crosspolymer, sodium hydroxide, myristic acid, myristyl alcohol, palmitic acid, ammonium polyacryloyldimethyl taurate, disodium EDTA, capryloyl glycine, caprylyl glycol, citric acid, xanthan gum, t-butyl alcohol, cetyl alcohol, tocopherol

Questions or comments?

1-888-LRP-LABO 1-888-577-5226

Monday - Friday (9 a.m. - 5 p.m. EST)